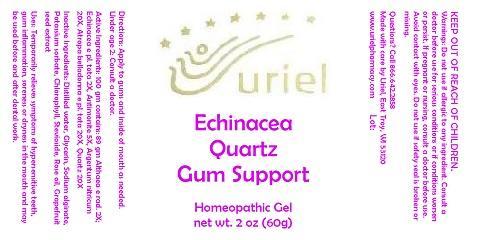 DRUG LABEL: Echinacea Quartz Gum Support
NDC: 48951-4019 | Form: GEL
Manufacturer: Uriel Pharmacy Inc.
Category: homeopathic | Type: HUMAN OTC DRUG LABEL
Date: 20140612

ACTIVE INGREDIENTS: ALTHAEA OFFICINALIS ROOT 2 [hp_X]/1 g; ECHINACEA, UNSPECIFIED 2 [hp_X]/1 g; ANTIMONY TRISULFIDE 5 [hp_X]/1 g; SILVER 20 [hp_X]/1 g; ATROPA BELLADONNA 20 [hp_X]/1 g; COLLOIDAL SILICON DIOXIDE 20 [hp_X]/1 g
INACTIVE INGREDIENTS: WATER; GLYCERIN; SODIUM ALGINATE; POTASSIUM SORBATE; CHLOROPHYLL; STEVIOSIDE; ROSE OIL; CITRUS PARADISI SEED

Echinacea Quartz Gum Support

DOSAGE AND ADMINISTRATION

Directions: Apply to gums and inside of mouth as needed.

ACTIVE INGREDIENT

Active Ingredients: 100 gm contains: 89 gm Althaea e rad. 2X; Echinacea e pl. tota 2X, Antimonite 5X, Argentum nitricum 20X, Atropa belladonna e pl. tota 20X, Quartz 20X

INACTIVE INGREDIENT

Inactive Ingredients: Distilled water, Glycerin, Sodium alginate, Potassium sorbate, Chlorophyll, Stevioside, Rose oil, Grapefruit seed extract

PURPOSE

Uses: Temporarily relieves symptoms of hypersensitive teeth, gum inflammation, soreness or dryness in the mouth and may be used before and after dental work.

KEEP OUT OF REACH OF CHILDREN.

WARNINGS

Warnings: Do not use if allergic to any ingredient. Consult a doctor before use for serious conditions or if conditions worsen or persist. If pregnant or nursing, consult a doctor before use. Avoid contact with eyes. Do not use if safety seal is broken or missing.

QUESTIONS

Questions? Call 866.642.2858 Made with care by Uriel, East Troy, WI 53120 www.urielpharmacy.com